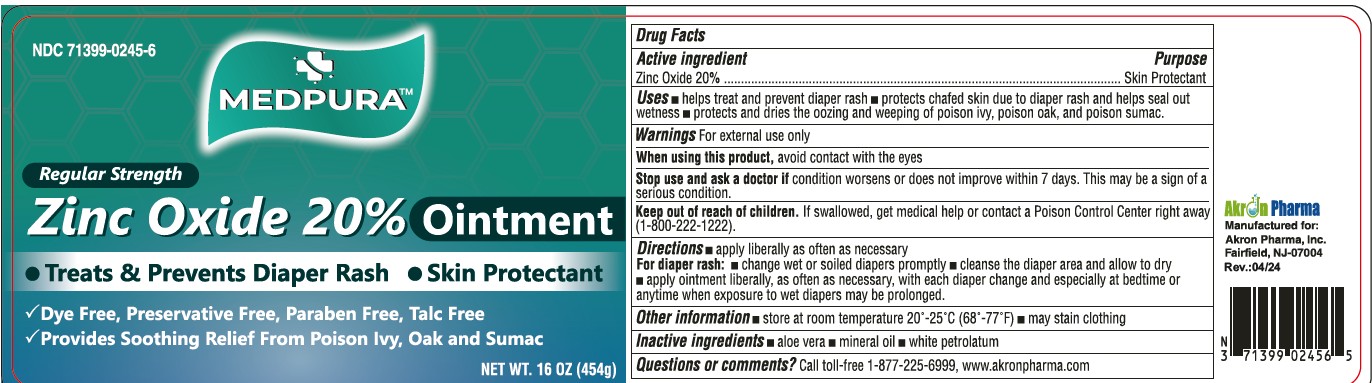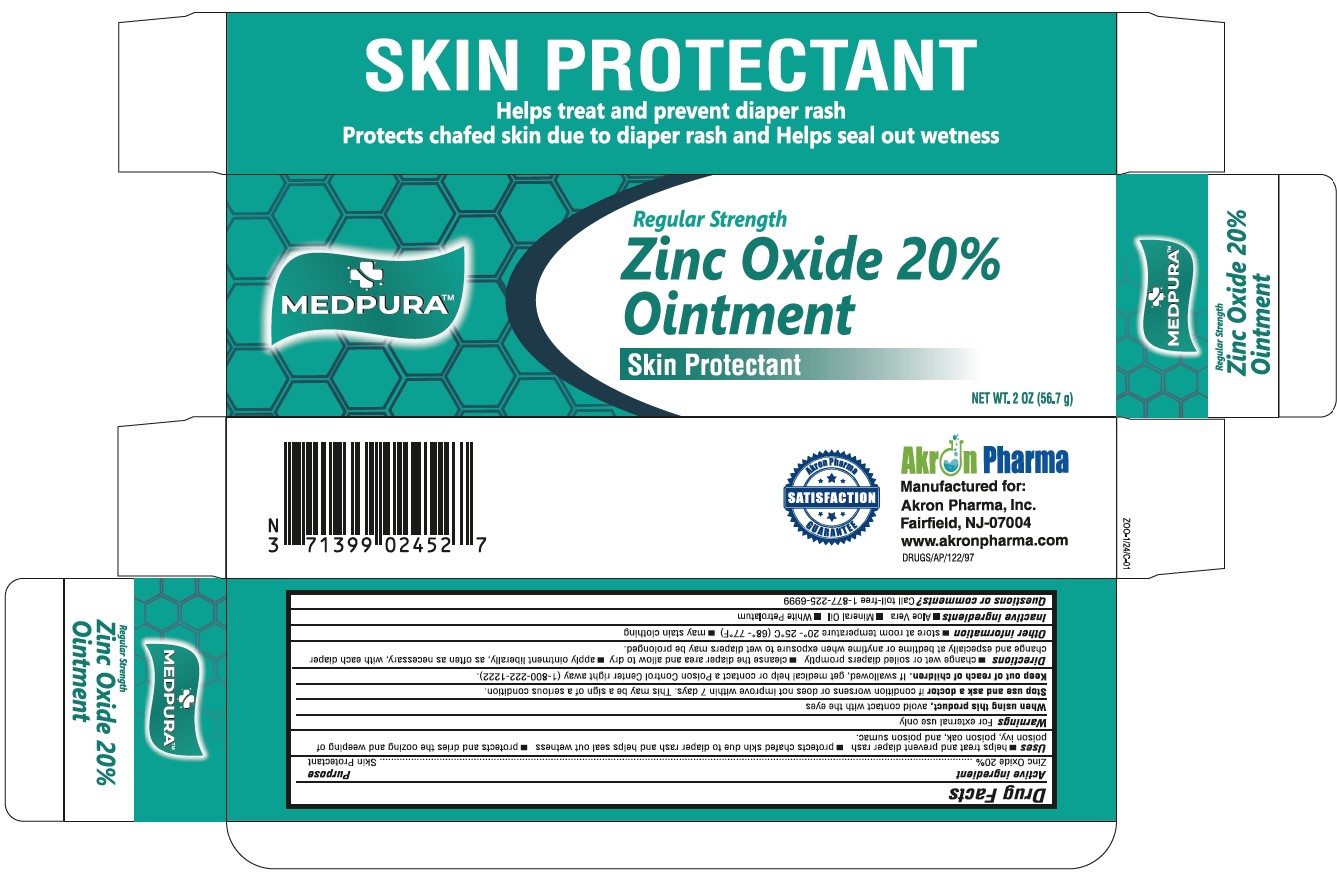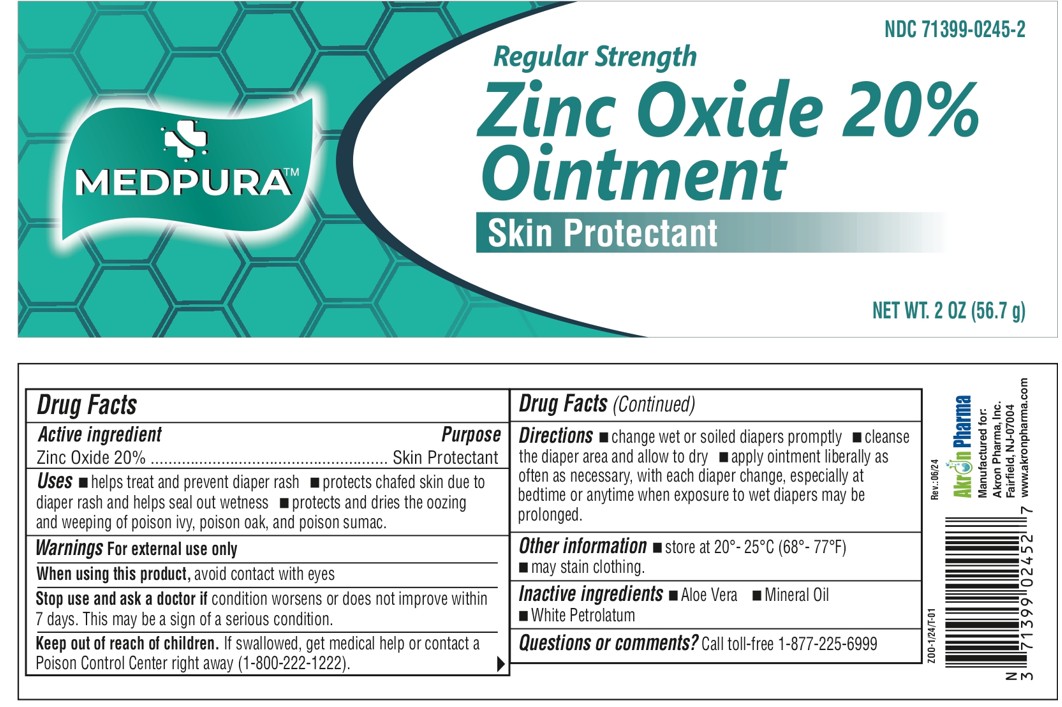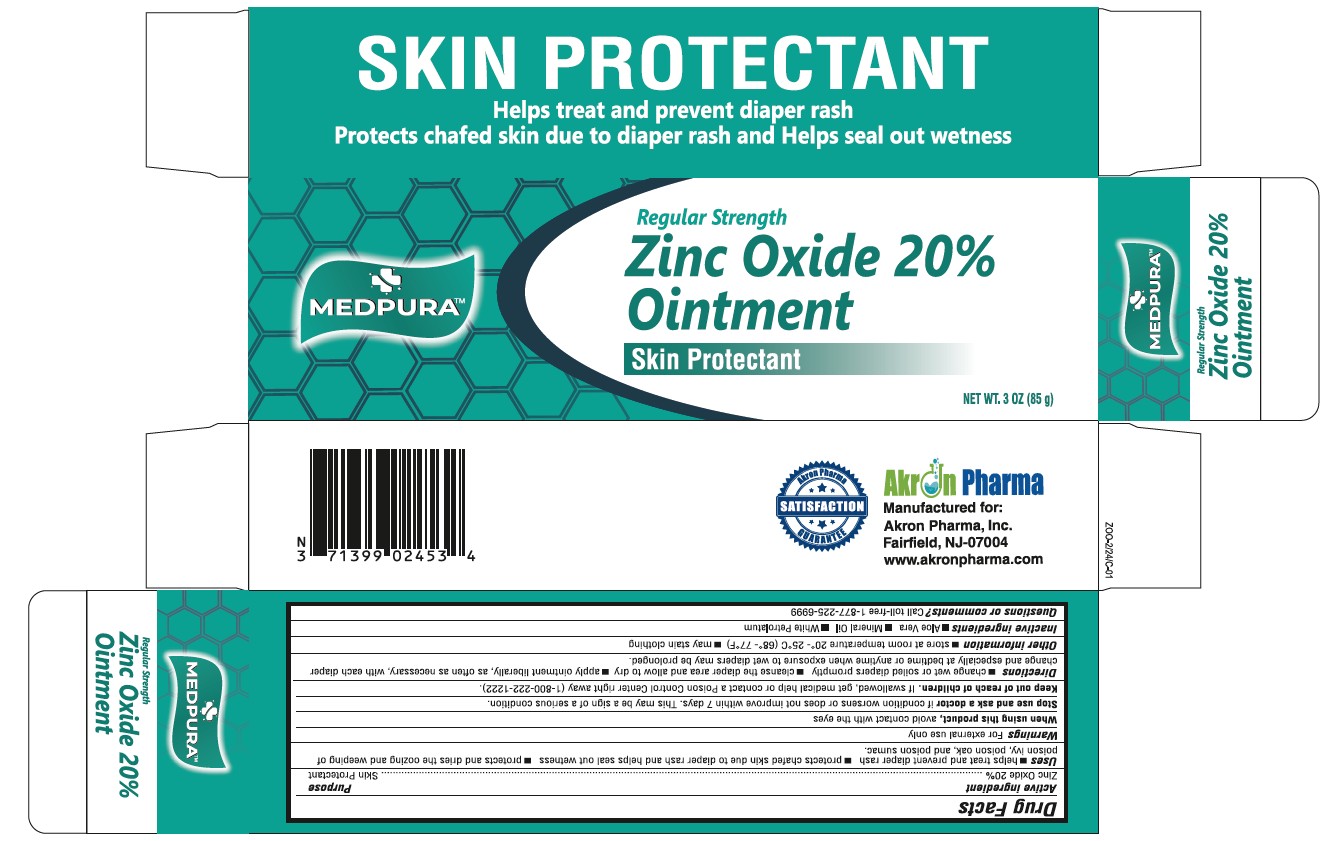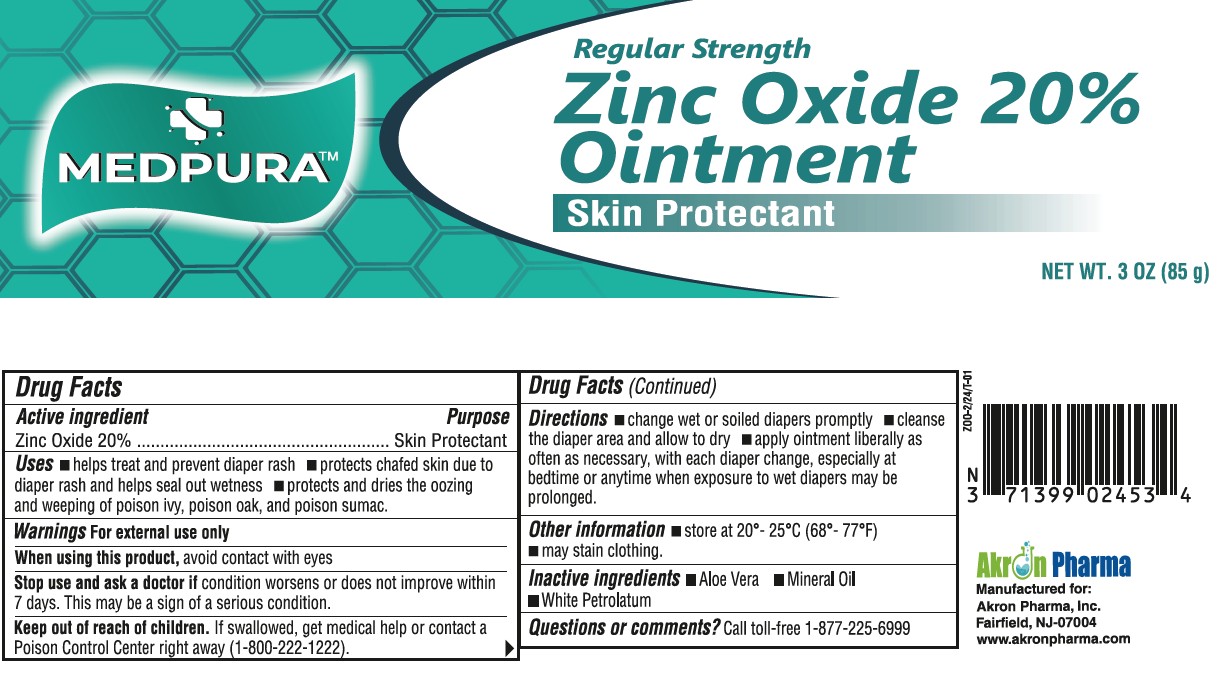 DRUG LABEL: Medpura Zinc Oxide 20%
NDC: 71399-0245 | Form: OINTMENT
Manufacturer: Akron Pharma Inc.
Category: otc | Type: HUMAN OTC DRUG LABEL
Date: 20260114

ACTIVE INGREDIENTS: ZINC OXIDE 20 g/100 g
INACTIVE INGREDIENTS: ALOE VERA LEAF; MINERAL OIL; WHITE PETROLATUM

MEDPURA
Zinc Oxide 20% Ointment
Regular Strength

Active Ingredient

Zinc Oxide 20%

Purpose

Skin Protectant

Uses

- helps treat and prevent diaper rash
- protects chafed skin due to diaper rash and helps seal out wetness
- protects and dries the oozing and weeping of poison ivy, poison oak, and poison sumac.

Warnings

For External Use Only

When using this product

avoid contact with the eyes

Stop use and ask a doctor if

if condition worsens or does not improve within 7 days. This may be a sign of a serious condition.

Keep out of reach of children

If swallowed, get medical help or contact a Poison Control Center right away (1-800-222-1222).

Directions

- change wet or soiled diapers promptly
- cleanse the diaper area and allow to dry
- apply ointment liberally, as often as necessary, with each diaper change and especially at bedtime or anytime when exposure to wet diapers may be prolonged.

Other Information

- store at room temperature 20˚-25˚C (68˚-77˚F)
- may stain clothing

Inactive Ingredients

alovera gel, mineral oil, white petrolatum

Questions and Comments?

Call toll-free 1-877-225-6999